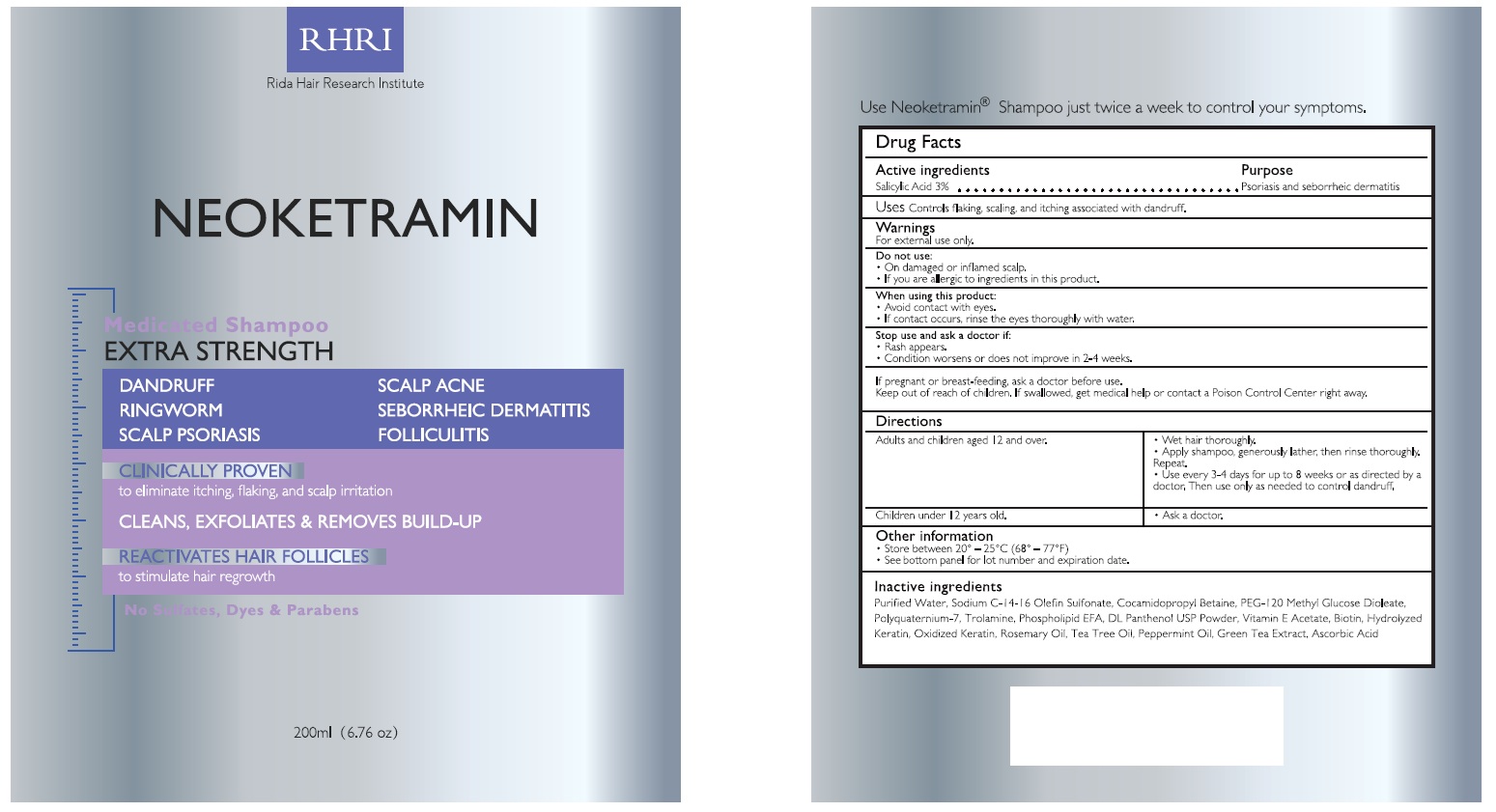 DRUG LABEL: Neoketramin Antifungal Dandruff Seborrheic Dermatitis  Psoriasis Treatment
NDC: 83004-019 | Form: LIQUID
Manufacturer: Rida LLC
Category: otc | Type: HUMAN OTC DRUG LABEL
Date: 20250306

ACTIVE INGREDIENTS: SALICYLIC ACID 3 g/100 mL
INACTIVE INGREDIENTS: WATER; SODIUM C14-16 OLEFIN SULFONATE; COCAMIDOPROPYL BETAINE; PEG-120 METHYL GLUCOSE DIOLEATE; POLYQUATERNIUM-7 (70/30 ACRYLAMIDE/DADMAC; 1600000 MW); TROLAMINE; PANTHENOL; .ALPHA.-TOCOPHEROL ACETATE; TEA TREE OIL; GREEN TEA LEAF; ASCORBIC ACID

Active Ingredient

Salicylic Acid 3%

Purpose

Psoriasis Dandruff
Seborrheic Dermatitis

Uses

Relieves and helps prevent recurrence of scalp:

- irritation
- itching
- redness
- flaking
- scaling due to psoriasis and seborrheic dermatitis

Directions

Adults and children aged 12 and over | - wet hair thoroughly - Apply shampoo, generously lather, then rinse thoroughly. Repeate - Use every 3-4 days for up to 8 weeks or as directed by a doctor. Then use only as needed to control; dandruff
Children under 12 years old. | Ask a doctor

Other information

- Store between 20°-25° C (68° -77° F)
- See bottom panel for lot number and expiration date.

Warnings

For external use only
Do not use

- On damaged or inflamed scalp
- If you are allergic to ingredients in this product

When using this product

- Avoid contact with eyes
- If contact occurs, rinse the eyes thoroughly with water.

Stop use and ask a doctor if:

- Rash appears
- Condition worsen or does not improve in 2-4 weeks.

If pregnant or breast-feeding, ask a doctor before use.

Keep out of reach of children. If swallowed, get medical help or contact a Poison Control Center right away.

Inactive ingredients

Ascorbic Acid, Cocamidopropyl Betaine, DL Panthenol USP Powder, Green Tea Extract, Linolemidopropyl PG-Dimonium Chloride Phosphate, PEG-120 Methyl Glucose Dioleate, Polyquaternium-7, Propylene Glycol, Puried Water, Sodium C-14-16 Olefin Sulfonate, Tea Tree Oil, Trolamine, Vitamin E Acetate